DRUG LABEL: INSTANT HAND SANITIZER WITH ALOE and VITAMIN E
NDC: 31190-300 | Form: SPRAY
Manufacturer: Shanghai Kejing Cleaning Products Co., Ltd.
Category: otc | Type: HUMAN OTC DRUG LABEL
Date: 20100415

ACTIVE INGREDIENTS: ALCOHOL 62 mL/100 mL
INACTIVE INGREDIENTS: FD&C BLUE NO. 1; FD&C YELLOW NO. 5; WATER

INSTANT HAND SANITIZER WITH ALOE and VITAMIN E 10mL

Active Ingredient Purpose

Ethyl Alcohol 62% ..........................Antimicrobial

PURPOSE

Uses: hand sanitizer to help reduce bacteria on the skin that could cause disease

recommended for repeated use.

Warnings

Flammable. Keep away from fire or flame.

For external use only

When using this product do not use in or near the eyes. In case of contact, rinse eyes thoroughly with water. Avoid contact with broken screen.

Stop use and ask a doctor if irritation or rash appears and lasts.

Keep out of reach of children. If swallowed, get medical help or contact a Poison Control Center right away.

DOSAGE AND ADMINISTRATION

Directions: spray enough product in your palm to thoroughly cover your hands; rub hands together briskly until dry; children under 6 years of age should be supervised when using this product; not recommended for infants.

STORAGE AND HANDLING

Store below 105 degree Fahrenheit (40 degree Celsius)

USER SAFETY WARNINGS

may discolor certain fabrics or surfaces; harmful to wood finishes and plastics

INACTIVE INGREDIENT

Inactive ingredients: aloe vera, blue #1, yellow #5, fragrance (parfum), PEG-18 dimethicone, tocopheryl acetate, water (aqua)

Questions or comments? 1-800-WALGREENS (1-800-925-4733)

DESCRIPTION

INSTANT Hand Sanitizer with aloe and vitamin E

Kills 99.9 percent of germs that may cause disease*

Use anywhere without the need for water

Leaves hands feeling soft and refreshed

*Effective at eliminating 99.99 percent of many common harmful germs and bacteria in as little as 15 seconds

Distributed by: Walgreen Co.,
200 Wilmot Rd., Deerfield, IL 60015-4616

Quality Guaranteed

100 percentSatisfaction on Guaranted with all Walgreens Products or Your Money Back

www.walgreens.com

Made in China

PACKAGE LABEL

INSTANT Hand Sanitizer with aloe and vitamin E

Easy-Control Pump Spray Mist

Kills 99.99 percent of Germs Instantly*

Fits in pocket or purse

Leaves hands feeling soft and refreshed

0.34 fl oz (10 mL)